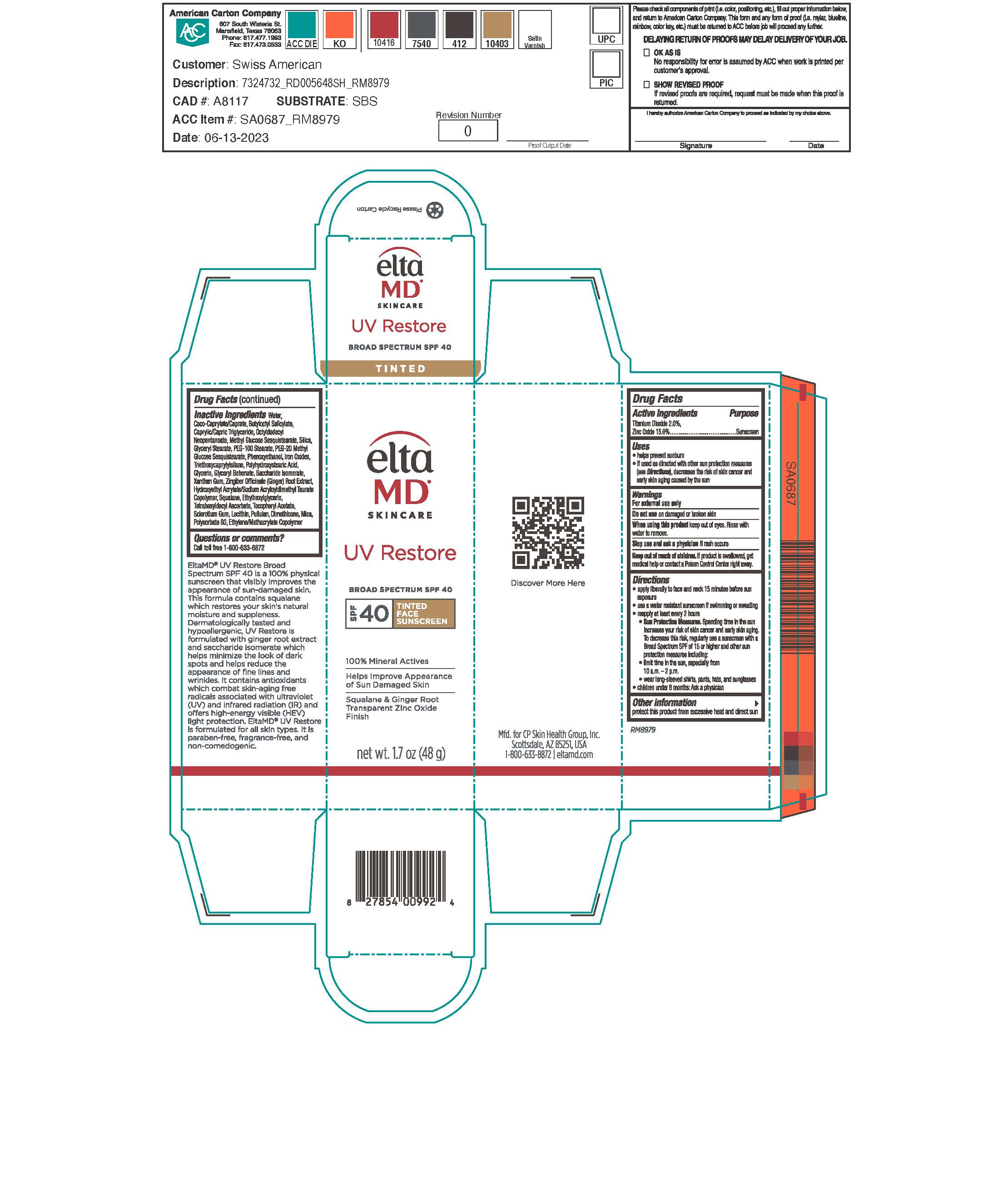 DRUG LABEL: EltaMD UV Restore Tinted
NDC: 72043-2640 | Form: LOTION
Manufacturer: CP Skin Health Group, Inc.
Category: otc | Type: HUMAN OTC DRUG LABEL
Date: 20240610

ACTIVE INGREDIENTS: TITANIUM DIOXIDE 20 g/1000 g; ZINC OXIDE 150 g/1000 g
INACTIVE INGREDIENTS: WATER; MEDIUM-CHAIN TRIGLYCERIDES; COCO-CAPRYLATE/CAPRATE; BUTYLOCTYL SALICYLATE; OCTYLDODECYL NEOPENTANOATE; METHYL GLUCOSE SESQUISTEARATE; GLYCERYL STEARATE SE; PEG-100 STEARATE; PEG-20 METHYL GLUCOSE SESQUISTEARATE; SILICON DIOXIDE; PHENOXYETHANOL; TRIETHOXYCAPRYLYLSILANE; POLYHYDROXYSTEARIC ACID (2300 MW); GLYCERIN; SACCHARIDE ISOMERATE; XANTHAN GUM; ZINGIBER CASSUMUNAR ROOT; HYDROXYETHYL ACRYLATE/SODIUM ACRYLOYLDIMETHYL TAURATE COPOLYMER (100000 MPA.S AT 1.5%); GLYCERYL MONOBEHENATE; SQUALANE; ETHYLHEXYLGLYCERIN; .ALPHA.-TOCOPHEROL ACETATE; TETRAHEXYLDECYL ASCORBATE; BETASIZOFIRAN; LECITHIN, SOYBEAN; PULLULAN; DIMETHICONE; POLYSORBATE 60; MICA; FERRIC OXIDE YELLOW; FERRIC OXIDE RED; FERROSOFERRIC OXIDE

EltaMD UV Restore Tinted

Warnings

For external use only. Do not use on damaged or broken skin. When using this product keep out of eyes. Rinse with water to remove. Stop use and ask a physician if rash occurs. If product is swallowed get medical help or contact a Poison Control Center right away.

Active Ingredients

Titanium Dioxide 2.0% Sunscreen
Zinc Oxide 15.0% Sunscreen

Keep out of reach of children

Uses

Helps prevent sunburn. If used as directed with other sun protection measure (See Directions), decreases the risk of skin cancer and early skin aging caused by the sun.

Uses

Helps prevent sunburn. If used as directed with other sun protection measure (See Directions), decreases the risk of skin cancer and early skin aging caused by the sun.

Directions

Apply liberally 15 minutes before sun exposure. Use a water-resistant sunscreen if swimming or sweating. Reapply at least every 2 hours. Sun Protection Measures: Spending time in the sun increases your risk of skin cancer and early skin aging. To decrease this risk, regularly use a sunscreen with a broad-spectrum SPF of 15 or higher and other sun protection measures including: limit time in the sun, especially from 10 am to 2 pm. Wear long-sleeve shirts, pants, hats, and sunglasses. Children under 6 months: ask a physician.

Other Information

Protect this product from excessive heat and direct sun.

Inactive Ingredients

water, coco-caprylate/caprate, butyloctyl salicylate, octyldodecyl neopentanoate, caprylic/capric triglyceride, methyl glucose sesquistearate, silica, glyceryl stearate, PEG-100 stearate, PEG-20 methyl glycose sesquisterate, phenoxyethanol, triethoxycaprylylsilane, polyhydroxystearic acid, glycerin, saccharide isomerate, glyceryl behenate, xanthan gum, zingiber officiale (ginger) root extract, hydroxyethyl acrylate/sodium acryloyldimethyl taurate copolymer, squalene, ethylhexylglycerin, tocopheryl acetate, sclerotium gum, lecithin, pulluan, dimethicone, polysorbate 60, ethylene/methacrylate copolymer, mica, iron oxides

Questions?

Call toll free 1-800-633-8872